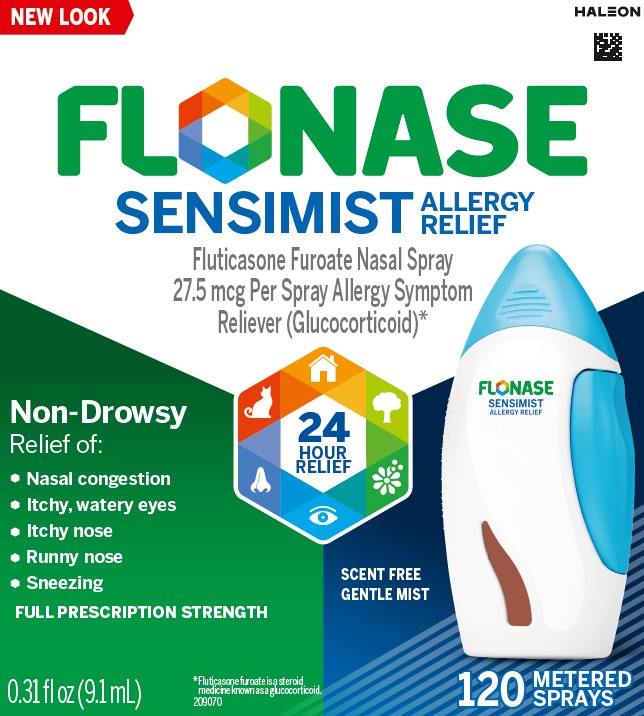 DRUG LABEL: FLONASE SENSIMIST
NDC: 0135-0615 | Form: SPRAY, METERED
Manufacturer: Haleon US Holdings LLC
Category: otc | Type: HUMAN OTC DRUG LABEL
Date: 20241219

ACTIVE INGREDIENTS: FLUTICASONE FUROATE 27.5 ug/1 1
INACTIVE INGREDIENTS: BENZALKONIUM CHLORIDE; CARBOXYMETHYLCELLULOSE SODIUM, UNSPECIFIED; ANHYDROUS DEXTROSE; EDETATE DISODIUM; MICROCRYSTALLINE CELLULOSE; POLYSORBATE 80; WATER

Drug Facts

Active ingredient (in each spray)

Fluticasone furoate 27.5 mcg (glucocorticoid)*

*read the Question & Answer Book

Purpose

Allergy symptom reliever

Uses

Temporarily relieves these symptoms of hay fever or other upper respiratory allergies:

- nasal congestion
- runny nose
- sneezing
- itchy nose
- itchy, watery eyes (for ages 12 and older)

Warnings

Only for use in the nose. Do not spray into your eyes or mouth.

Do not use

- in children under 2 years of age
- to treat asthma
- if you have an injury or surgery to your nose that is not fully healed
- if you have ever had an allergic reaction to this product or any of the ingredients

Ask a doctor before use if you

have or had glaucoma or cataracts

Ask a doctor or pharmacist before use if you are taking

- medicine for HIV infection (such as ritonavir)
- a steroid medicine for asthma, allergies or skin rash
- ketoconazole pills (medicine for fungal infection)

When using this product

- the growth rate of some children may be slower
- stinging or sneezing may occur for a few seconds right after use
- do not share this bottle with anyone else as this may spread germs
- remember to tell your doctor about all the medicines you take, including this one

Stop use and ask a doctor if

- you have, or come into contact with someone who has, chicken pox, measles or tuberculosis
- your symptoms do not get better within 7 days of starting use or you get new symptoms such as severe facial pain or thick nasal discharge. You may have something more than allergies, such as an infection.
- you get a constant whistling sound from your nose. This may be a sign of damage inside your nose.
- you get an allergic reaction to this product. Seek medical help right away.
- you get new changes to your vision that develop after starting this product
- you have severe or frequent nosebleeds

If pregnant or breast-feeding,

ask a health professional before use.

Keep out of reach of children.

In case of overdose, get medical help or contact a Poison Control Center right away.

Directions

- read the Quick Start Guide for how to:
  - shake vigorously before each use
  - prime the bottle
  - use the spray
  - sniff gently after each spray
- clean the spray nozzle with a clean dry tissue
- use this product only once a day
- do not use more than directed

ADULTS AND CHILDREN 12 YEARS OF AGE AND OLDER

- Week 1 – use 2 sprays in each nostril once daily
- Week 2 through 6 months – use 1 or 2 sprays in each nostril once daily, as needed to treat your symptoms
- After 6 months of daily use – ask your doctor if you can keep using

CHILDREN 2 TO 11 YEARS OF AGE

- the growth rate of some children may be slower while using this product. Children should use for the shortest amount of time necessary to achieve symptom relief. Talk to your child’s doctor if your child needs to use the spray for longer than two months a year.
- an adult should supervise use
- use 1 spray in each nostril once daily

CHILDREN UNDER 2 YEARS OF AGE

- do not use

Other information

- you may start to feel relief the first day and full effect after several days of regular, once-a-day use
- store between 15° – 30°C (59° – 86°F)
- do not refrigerate or freeze
- keep this label and enclosed materials. They contain important additional information.

Inactive ingredients

benzalkonium chloride solution, carboxymethylcellulose sodium, dextrose anhydrous, edetate disodium, microcrystalline cellulose, polysorbate 80, purified water

Questions or comments?

call toll-free 1-844-FLONASE (1-844-356-6273)

Generic Section

FLONASE SENSIMIST ALLERGY RELIEF

What problems can FLONASE SENSIMIST Allergy Relief help with?

FLONASE SENSIMIST Allergy Relief helps relieve a broad range of uncomfortable symptoms like congestion and itchy eyes*.

Nasal symptoms

Eye symptoms*

*for ages 12 and older.

These symptoms can be triggered by allergens like pollen, mold, dust or pet dander.

Outdoor allergens

Animal allergens

Indoor allergens

IMPORTANT – Peel here for complete Drug Facts label. Children 2-11: do not use for more than 2 months a year.

Be sure to read the Quick Start Guide and Question & Answer Book inside package

TAMPER-EVIDENT features for your protection. The product is packaged in a sealed plastic container. The bottle is housed within a plastic dispenser that prevents direct access to the bottle. Do not use if the container or any part of the plastic dispenser, including the dispenser bottom, is damaged or broken.

Principal Display Panel

FLONASE

SENSIMIST

ALLERGY RELIEF

Fluticasone Furoate Nasal Spray 27.5 mcg Per Spray Allergy Symptom Reliever (Glucocorticoid)*

Non-Drowsy Relief of:

- Nasal congestion
- itchy, watery eyes
- Itchy nose
- Runny nose
- Sneezing

FULL PRESCRIPTION STRENGTH

24 HOUR RELIEF

120 METERED SPRAYS

*Fluticasone furoate is a steroid medicine known as a glucocorticoid.

0.31 fl oz (9.1 mL)